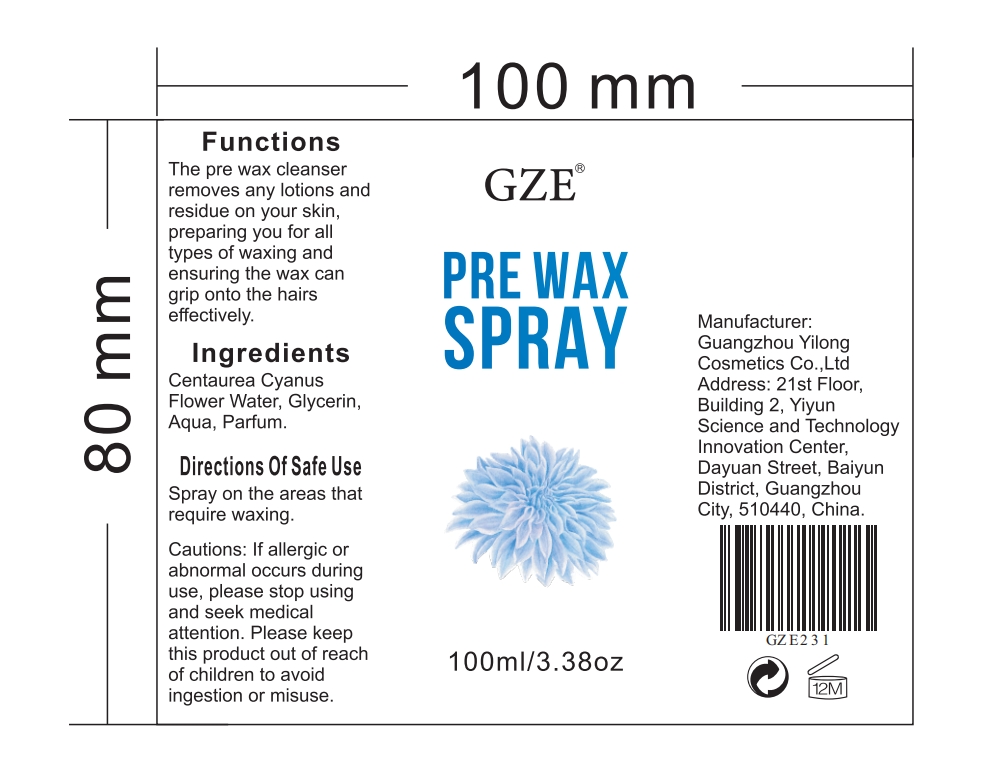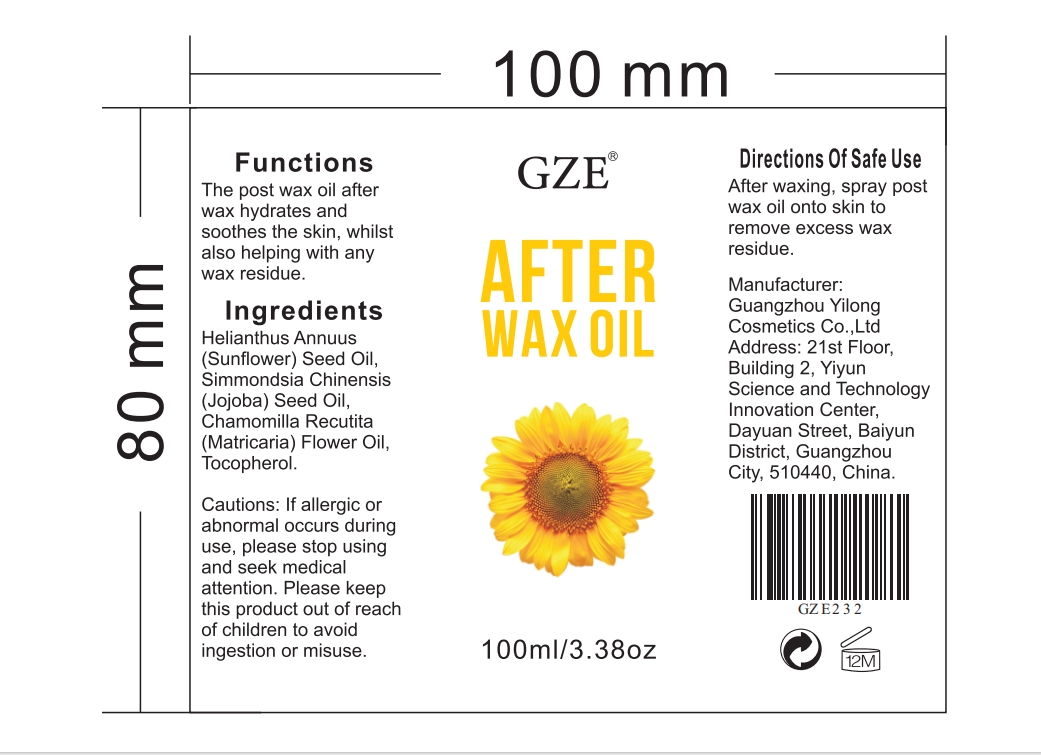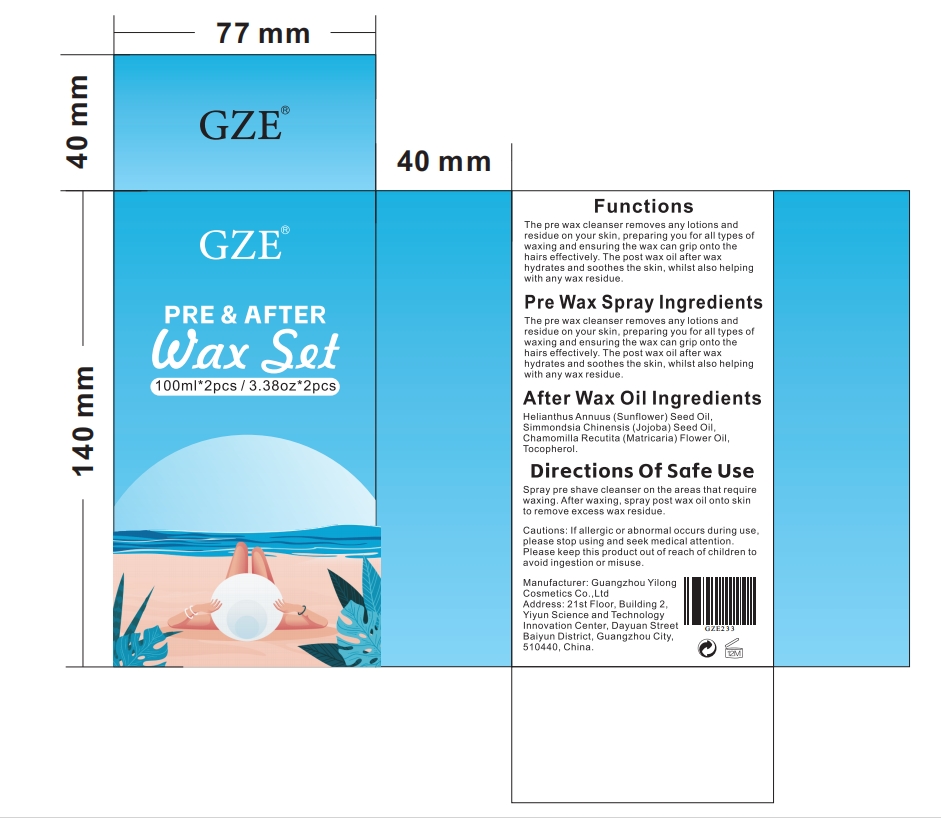 DRUG LABEL: GZE Pre After Wax Set
NDC: 83566-233 | Form: LIQUID
Manufacturer: Guangzhou Yilong Cosmetics Co.,Ltd.
Category: otc | Type: HUMAN OTC DRUG LABEL
Date: 20240601

ACTIVE INGREDIENTS: JOJOBA OIL 20 g/100 mL; SUNFLOWER SEED 15 g/100 mL; CENTAUREA CYANUS FLOWER 12.5 g/100 mL; MATRICARIA CHAMOMILLA FLOWERING TOP OIL 20 g/100 mL
INACTIVE INGREDIENTS: TOCOPHEROL; GLYCERIN; WATER; PARFUMIDINE

GZE Pre After Wax Set

ACTIVE INGREDIENT

JOJOBA OIL
MATRICARIA CHAMOMILLA FLOWERING TOP OIL
CENTAUREA CYANUS FLOWER
SUNFLOWER SEED

INACTIVE INGREDIENT

TOCOPHEROL
GLYCERIN
WATER
PARFUMIDINE

PURPOSE

The pre wax cleanser removes any lotions and residue on your skin, preparing you for all types of waxing and ensuring the wax can grip onto the hairs effectively, The post wax oil after wax hydrates and soothes the skin, whilst also helping with any wax residue.

INDICATIONS AND USAGE

Spray pre shave cleanser on the areas that require waxing.After waxing,spray post wax oil onto skinto remove excess wax residue.

WARNINGS

For external use only.

Stop use and ask a doctor if rash occurs.

Do not use on damaged or broken skin.

When using this product keep out of eyes. Rinse with water to remove.

Keep out of reach of children. If swallowed, get medical help or contact a Poison Control Center right away.

DOSAGE AND ADMINISTRATION

Spray pre shave cleanser on the areas that require waxing.After waxing,spray post wax oil onto skinto remove excess wax residue.